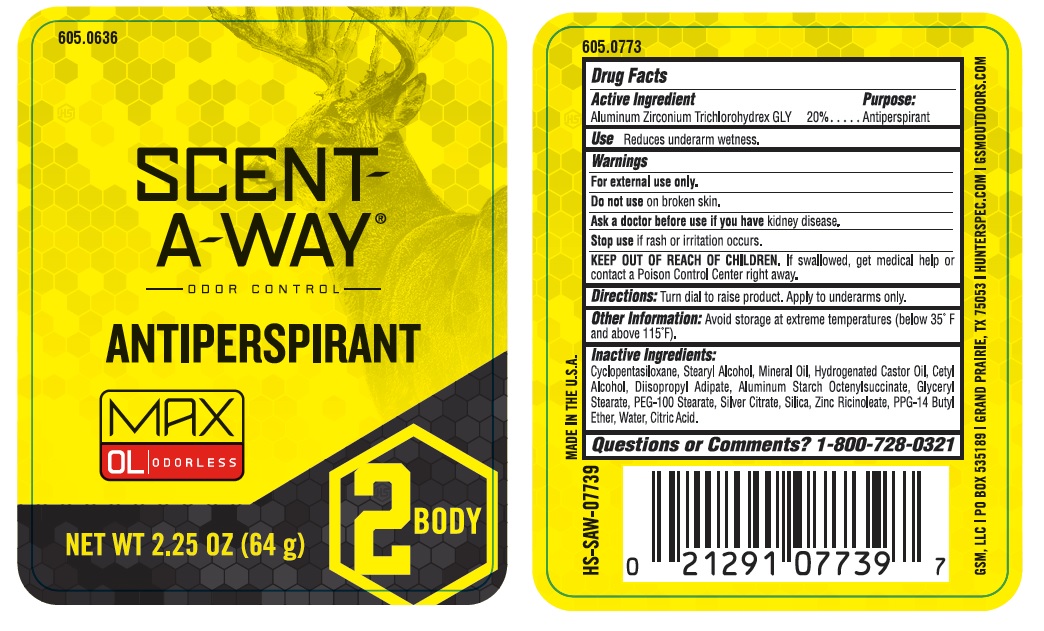 DRUG LABEL: Scent-A-Way Odor Control Max
NDC: 10889-418 | Form: STICK
Manufacturer: VVF Kansas Services LLC
Category: otc | Type: HUMAN OTC DRUG LABEL
Date: 20221229

ACTIVE INGREDIENTS: ALUMINUM ZIRCONIUM TRICHLOROHYDREX GLY 12.8 g/64 g
INACTIVE INGREDIENTS: CYCLOMETHICONE 5; STEARYL ALCOHOL; MINERAL OIL; HYDROGENATED CASTOR OIL; SILVER CITRATE; ANHYDROUS CITRIC ACID; PEG-100 STEARATE; ZINC RICINOLEATE; TALC; DIISOPROPYL ADIPATE; ALUMINUM STARCH OCTENYLSUCCINATE; GLYCERYL STEARATE SE; SILICON DIOXIDE; CETYL ALCOHOL; PPG-14 BUTYL ETHER

Scent-A-Way Odor Control Max
Anti-Perspirant
Odorless

Active Ingredient

Aluminum Zirconium Trichlorohydrex GLY 20%

Purpose

Antiperspirant

Use

Reduces underarm wetness.

Warnings

For external use only.

Do not use on broken skin.

Ask a doctor before use if you have kidney disease.

Stop use if rash or irritation occurs.

KEEP OUT OF REACH OF CHILDREN.

If swallowed, get medical help or contact a Poison Control Center right away.

Directions:

Turn dial to raise product. Apply to underarm only.

Other information:

Avoid storage at extreme temperatures (below 35°F and above 115°F).

Inactive Ingredients

Cyclopentasiloxane, Stearyl Alcohol, Mineral Oil, Hydrogenated Castor Oil, Cetyl

Alcohol, Diisopropyl Adipate, Aluminum Starch Octenylsuccinate, Glyceryl

Stearate, PEG-100 Stearate, Silver Citrate, Silica, Zinc Ricinoleate, PPG-14 Butyl

Ether, Water, Citric Acid.

Questions or Comments?

1-800-728-0321

GSM, LLC

PO BOX 535189

GRAND PRAIRIE, TX 75053

HUNTERSPEC.COM

GSMOUTDOORS.COM

MADE IN THE U.S.A.

UPC: 0-21291-07739-7

HS-SAW-07739